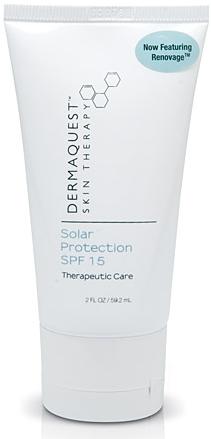 DRUG LABEL: Dermaquest Skin Therapy Solar Protection SPF 15
NDC: 62742-4052 | Form: CREAM
Manufacturer: Allure Labs, Inc.
Category: otc | Type: HUMAN OTC DRUG LABEL
Date: 20100820

ACTIVE INGREDIENTS: ZINC OXIDE 95 mg/1 mL

Drug Facts

INDICATIONS AND USAGE

Optimal for daily use, this state-of-the-art, broad-spectrum sunscreen contains Zinc Oxide to help protect against the damaging effects of UVA and UVB rays. Cosmetically elegant and hydrating, this sunscreen id rapidly absorbed into the skin and is ideal for acne-prone akin and post-professional treatments.

DIRECTIONS:

Apply sunscreen in the AM to fingertips and gently massage into the skin. Reapply if needed.

ACTIVE INGREDIENT:

Zinc Oxide 9.5%

INACTIVE INGREDIENTS:
Water (Aqua), Cyclomethicone, Caprylic/Capric Triglyceride (and) Teprenone, Glycerin, Glyceryl Stearate (and) PEG-100 Stearate, Date (Phoenix dactylefera) Extract (and) Sodium Lactate, Sorbitol, Imperata cylidrica (root) Extract, Caprylyl Glycol, Sorbitan Stearate, Lecithin, Arabidopsis Extract, Plankton Extract, Xanthan Gum, Carbomer, Ascorbyl Palmitate (Viatmin C), Tocopheryl acetate (Viatmin E), Citric Acid, Disodium EDTA.

PACKAGE LABEL

DISTRIBUTOR:
DeramQuest Skin Therapy
Hayward, CA 94544
dermaquestinc.com
Image of 2 fl oz size tube:
Solar Protection SPF 15